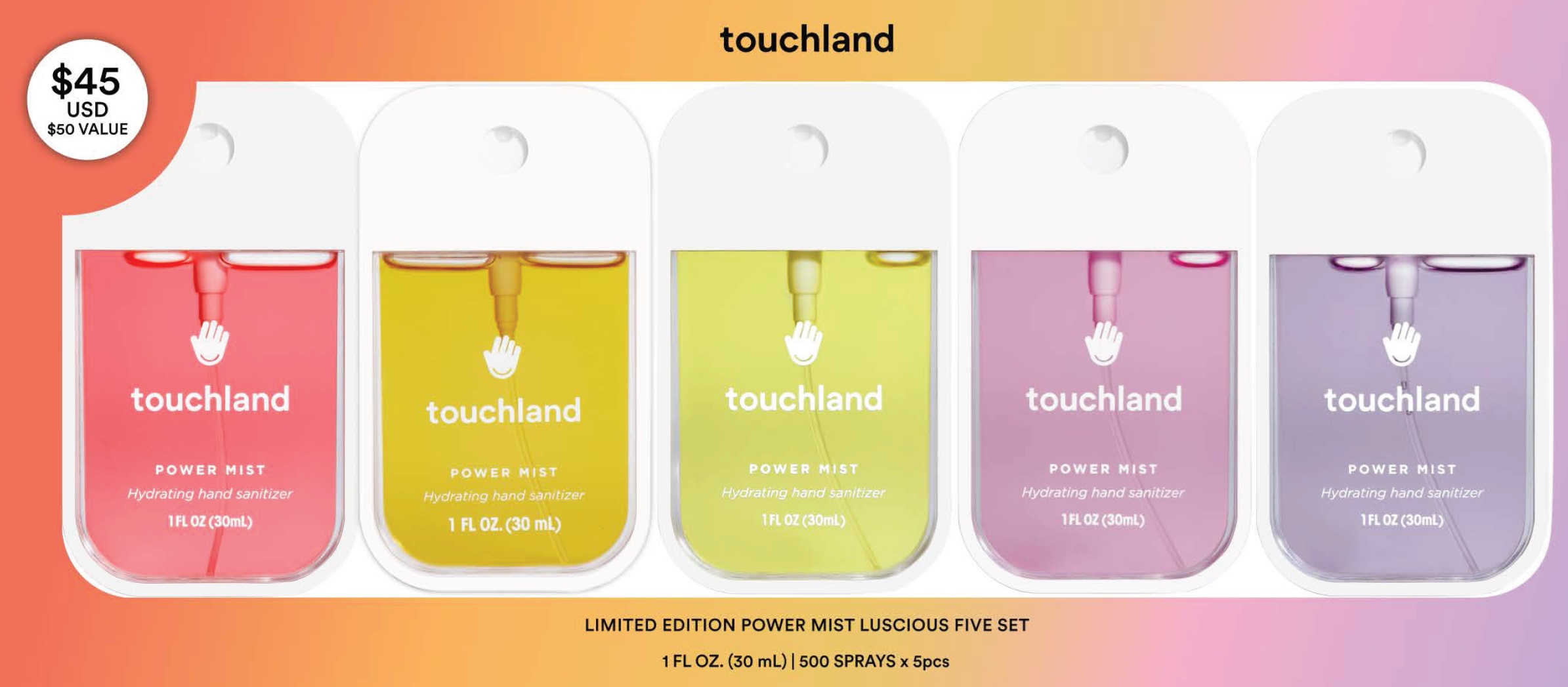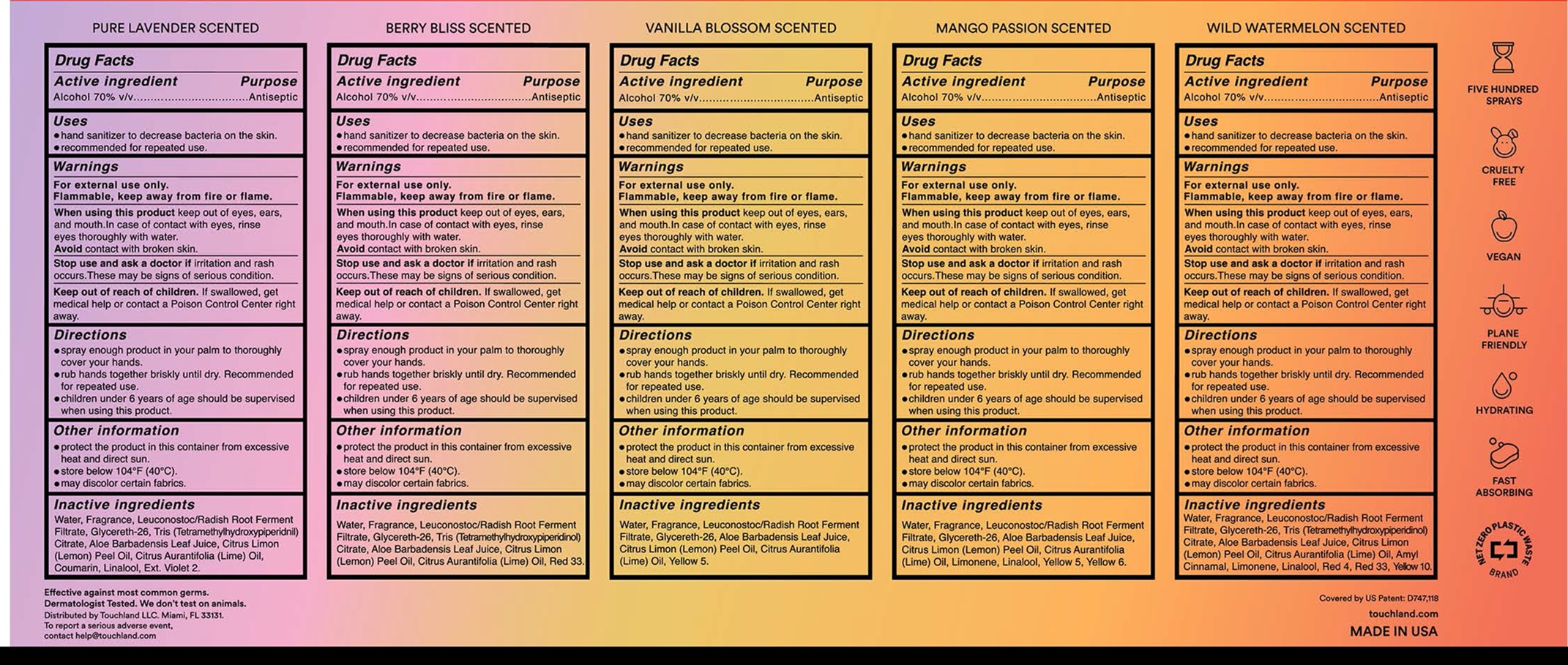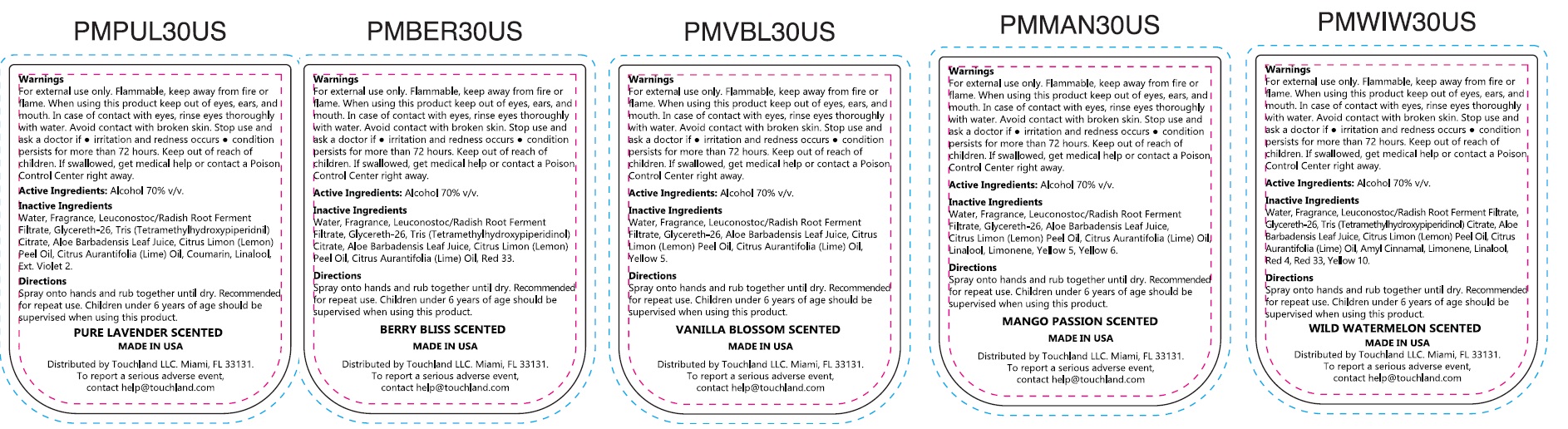 DRUG LABEL: Touchland Limited Edition Power Mist Luscious Five Set
NDC: 72033-133 | Form: KIT | Route: TOPICAL
Manufacturer: TOUCHLAND LLC
Category: otc | Type: HUMAN OTC DRUG LABEL
Date: 20240530

ACTIVE INGREDIENTS: ALCOHOL 70 mL/100 mL; ALCOHOL 70 mL/100 mL; ALCOHOL 70 mL/100 mL; ALCOHOL 70 mL/100 mL; ALCOHOL 70 mL/100 mL
INACTIVE INGREDIENTS: WATER; LEUCONOSTOC/RADISH ROOT FERMENT FILTRATE; GLYCERETH-26; ALOE VERA LEAF; LEMON OIL, COLD PRESSED; LIME OIL, COLD PRESSED; COUMARIN; LINALOOL, (+/-)-; EXT. D&C VIOLET NO. 2; WATER; LEUCONOSTOC/RADISH ROOT FERMENT FILTRATE; GLYCERETH-26; TRIS(TETRAMETHYLHYDROXYPIPERIDINOL) CITRATE; ALOE VERA LEAF; LEMON OIL, COLD PRESSED; LIME OIL, COLD PRESSED; D&C RED NO. 33; WATER; LEUCONOSTOC/RADISH ROOT FERMENT FILTRATE; GLYCERETH-26; ALOE VERA LEAF; LEMON OIL, COLD PRESSED; LIME OIL, COLD PRESSED; FD&C YELLOW NO. 5; WATER; LEUCONOSTOC/RADISH ROOT FERMENT FILTRATE; GLYCERETH-26; ALOE VERA LEAF; LEMON OIL, COLD PRESSED; LIME OIL, COLD PRESSED; LIMONENE, (+)-; LINALOOL, (+/-)-; FD&C YELLOW NO. 5; FD&C YELLOW NO. 6; WATER; LEUCONOSTOC/RADISH ROOT FERMENT FILTRATE; GLYCERETH-26; TRIS(TETRAMETHYLHYDROXYPIPERIDINOL) CITRATE; ALOE VERA LEAF; LEMON OIL, COLD PRESSED; LIME OIL, COLD PRESSED; LIMONENE, (+)-; LINALOOL, (+/-)-; FD&C RED NO. 4; D&C RED NO. 33; D&C YELLOW NO. 10

Touchland Limited Edition Power Mist Luscious Five Set

Active ingredient

Alcohol 70% v/v

Purpose

Antiseptic

Uses

- hand sanitizer to decrease bacteria on the skin.
- recommended for repeated use.

Warnings

For external use only.

Flammable, keep away from fire or flame.

When using this product

keep out of eyes, ears, and mouth. In case of contact with eyes, rinse eyes thoroughly with water. Avoid contact with broken skin.

Stop use and ask a doctor if

irritation and rash occurs. These may be signs of serious condition.

Keep out of reach of children.

If swallowed, get medical help or contact a Poison Control Center right away.

Directions

- spray enough product in your palm to thoroughly cover your hands.
- rub hands together briskly until dry. Recommended for repeated use.
- children under 6 years of age should be supervised when using this product.

Other information

- protect the product in this container from excessive heat and direct sun.
- store below 104°F (40°C).
- may discolor certain fabrics.

Inactive ingredients

Water, Fragrance, Leuconostoc/Radish Root Ferment Filtrate, Glycereth-26, Tris (Tetramethylhydroxypiperidnil) Citrate, Aloe Barbadensis Leaf Juice, Citrus Limon (Lemon) Peel Oil, Citrus Aurantifolia (Lime) Oil, Coumarin, Linalool, Ext. Violet 2.

Active ingredient

Alcohol 70% v/v

Purpose

Antiseptic

Uses

- hand sanitizer to decrease bacteria on the skin.
- recommended for repeated use.

Warnings

For external use only.

Flammable, keep away from fire or flame.

When using this product

keep out of eyes, ears, and mouth. In case of contact with eyes, rinse eyes thoroughly with water. Avoidcontact with broken skin.

Stop use and ask a doctor if

irritation and rash occurs. These may be signs of serious condition.

Keep out of reach of children.

If swallowed, get medical help or contact a Poison Control Center right away.

Directions

- spray enough product in your palm to thoroughly cover your hands.
- rub hands together briskly until dry. Recommended for repeated use.
- children under 6 years of age should be supervised when using this product.

Other information

- protect the product in this container from excessive heat and direct sun.
- store below 104°F (40°C).
- may discolor certain fabrics.

Inactive ingredients

Water, Fragrance, Leuconostoc/Radish Root Ferment Filtrate, Glycereth-26, Tris (Tetramethylhydroxypiperidinol) Citrate, Aloe Barbadensis Leaf Juice, Citrus Limon (Lemon) Peel Oil, Citrus Aurantifolia (Lime) Oil, Red 33.

Active ingredient

Alcohol 70% v/v

Purpose

Antiseptic

Uses

- hand sanitizer to decrease bacteria on the skin.
- recommended for repeated use.

Warnings

For external use only.

Flammable, keep away from fire or flame.

When using this product

keep out of eyes, ears, and mouth. In case of contact with eyes, rinse eyes thoroughly with water. Avoidcontact with broken skin.

Stop use and ask a doctor if

irritation and rash occurs. These may be signs of serious condition.

Keep out of reach of children.

If swallowed, get medical help or contact a Poison Control Center right away.

Directions

- spray enough product in your palm to thoroughly cover your hands.
- rub hands together briskly until dry. Recommended for repeated use.
- children under 6 years of age should be supervised when using this product.

Other information

- protect the product in this container from excessive heat and direct sun.
- store below 104°F (40°C).
- may discolor certain fabrics.

Inactive ingredients

Water, Fragrance, Leuconostoc/Radish Root Ferment Filtrate, Glycereth-26, Aloe Barbadensis Leaf Juice, Citrus Limon (Lemon) Peel Oil, Citrus Aurantifolia (Lime) Oil, Yellow 5.

Active ingredient

Alcohol 70% v/v

Purpose

Antiseptic

Uses

- hand sanitizer to decrease bacteria on the skin.
- recommended for repeated use.

Warnings

For external use only.
Flammable, keep away from fire or flame.

When using this product

keep out of eyes, ears, and mouth. In case of contact with eyes, rinse eyes thoroughly with water. Avoidcontact with broken skin.

Stop use and ask a doctor if

irritation and rash occurs. These may be signs of serious condition.

Keep out of reach of children.

If swallowed, get medical help or contact a Poison Control Center right away.

Directions

- spray enough product in your palm to thoroughly cover your hands.
- rub hands together briskly until dry. Recommended for repeated use.
- children under 6 years of age should be supervised when using this product.

Other information

- protect the product in this container from excessive heat and direct sun.
- store below 104°F (40°C).
- may discolor certain fabrics.

Inactive ingredients

Water, Fragrance, Leuconostoc/Radish Root Ferment Filtrate, Glycereth-26, Aloe Barbadensis Leaf Juice, Citrus Limon (Lemon) Peel Oil, Citrus Aurantifolia (Lime) Oil, Limonene, Linalool, Yellow 5, Yellow 6.

Active ingredient

Alcohol 70% v/v

Purpose

Antiseptic

Uses

- hand sanitizer to decrease bacteria on the skin.
- recommended for repeated use.

Warnings

For external use only.
Flammable, keep away from fire or flame.

When using this product

keep out of eyes, ears, and mouth. In case of contact with eyes, rinse eyes thoroughly with water. Avoidcontact with broken skin.

Stop use and ask a doctor if

irritation and rash occurs. These may be signs of serious condition.

Keep out of reach of children.

If swallowed, get medical help or contact a Poison Control Center right away.

Directions

- spray enough product in your palm to thoroughly cover your hands.
- rub hands together briskly until dry. Recommended for repeated use.
- children under 6 years of age should be supervised when using this product.

Other information

- protect the product in this container from excessive heat and direct sun.
- store below 104°F (40°C).
- may discolor certain fabrics.

Inactive ingredients

Water, Fragrance, Leuconostoc/Radish Root Ferment Filtrate, Glycereth-26, Tris (Tetramethylhydroxypiperidinol) Citrate, Aloe Barbadensis Leaf Juice, Citrus Limon (Lemon) Peel Oil, Citrus Aurantifolia Lime Oil, Amyl Cinnamal, Limonene, Linalool, Red 4, Red 33, Yellow 10.